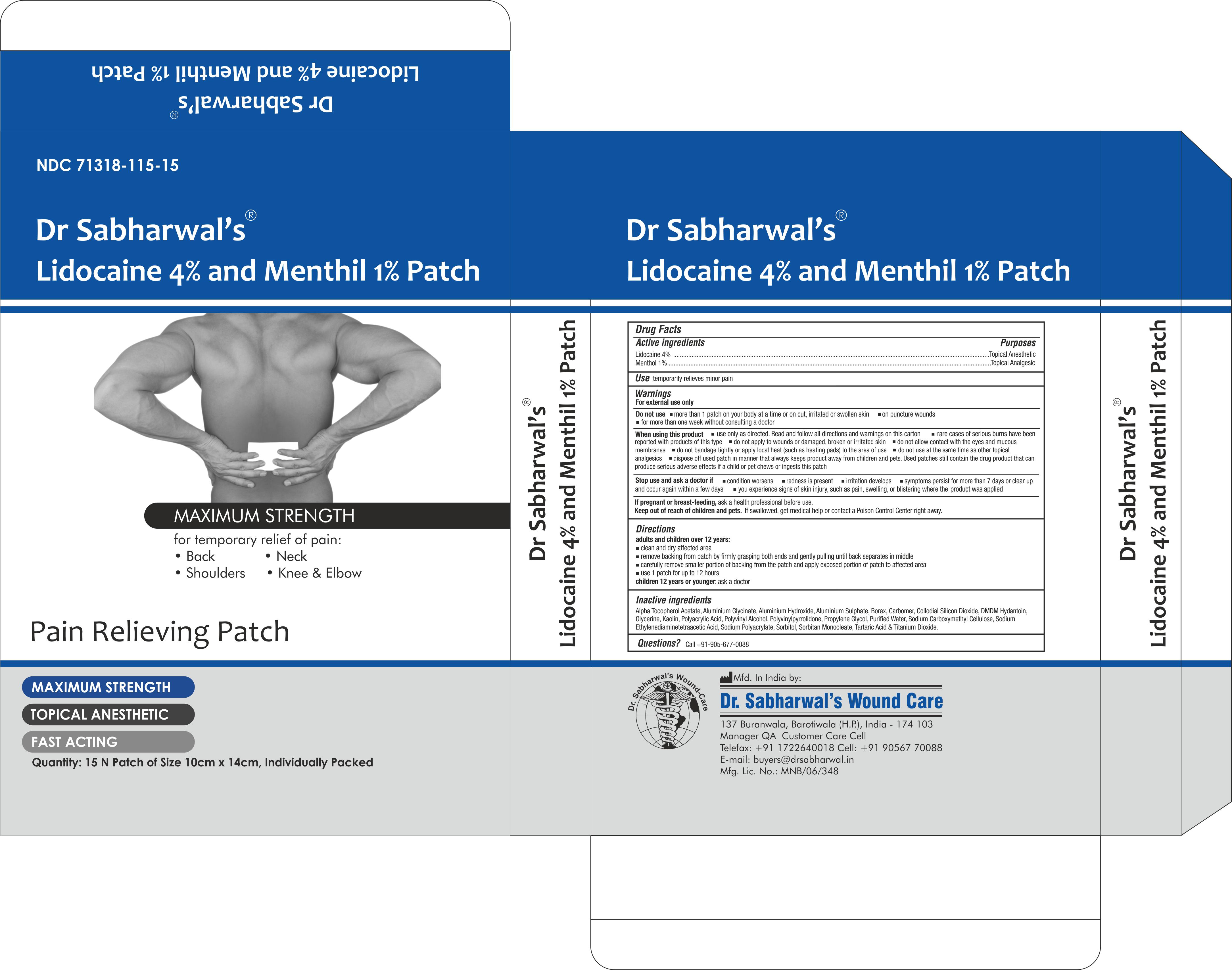 DRUG LABEL: Dr Sabharwals
NDC: 71318-115 | Form: PATCH
Manufacturer: Dr. Sabharwal's Wound Care
Category: otc | Type: HUMAN OTC DRUG LABEL
Date: 20260123

ACTIVE INGREDIENTS: LIDOCAINE 224 mg/1 1; MENTHOL 56 mg/1 1
INACTIVE INGREDIENTS: ALUMINIUM SULFATE OCTADECAHYDRATE; WATER; SORBITAN MONOOLEATE; POLYACRYLIC ACID (250000 MW); KAOLIN; ALPHA-TOCOPHEROL ACETATE; DMDM HYDANTOIN; SODIUM POLYACRYLATE (8000 MW); POLYVINYL ALCOHOL (100000 MW); TARTARIC ACID; TITANIUM DIOXIDE; GLYCERIN; ALUMINUM HYDROXIDE; PROPYLENE GLYCOL; EDETATE DISODIUM; POVIDONE; CARBOXYMETHYLCELLULOSE SODIUM; BORAX; SILICON DIOXIDE; BUTYLATED HYDROXYTOLUENE; DIHYDROXYALUMINUM AMINOACETATE

ACTIVE INGREDIENT

Lidocaine 4%

Menthol 1%

PURPOSE

Topical Anesthetic

INTENDED USE OF THE DEVICE

Temporarily relieves minor pain associated with: arthritis, simple backache, bursitis, tendonitis, muscle strains, sprains & bruises.

WARNINGS

For external use only

DO NOT USE

- more than 1 patch on your body at a time or on cut, irritated or swollen skin
- on puncture wounds
- for more than one week without consulting a doctor

WHEN USING

- use only as directed. Read and follow all directions and warnings on this label.
- do not allow contact with the eyes
- do not bandage tightly or apply local heat (such as heating pads) to the area of use
- do not use at the same time as other topical analgesics
- dispose of used patch in manner that always keeps product away from children or pets. Used patches still contain the drug product that can produce serious adverse effects if a child or pet chews or ingests this patch.

ASK DOCTOR

- condition worsens
- redness is present
- irritation develops
- symptoms persist for more than 7 days or clear up and occur again within a few days
- you experience signs of skin injury, such as pain, swelling, or blistering where the product was applied

PREGNANCY OR BREAST FEEDING

ask a health professional before use.

KEEP OUT OF REACH OF CHILDREN

If swallowed, get medical help or contact a Poison Control Center right away.

INSTRUCTIONS FOR USE

Adults and children over 12 years:

- clean and dry affected area
- remove backing from patch by firmly grasping both ends and gently pulling until backing separates in middle
- carefully remove smaller portion of backing from patch and apply exposed portion of patch to affected area
- once exposed portion of patch is positioned, carefully remove remaining backing to completely apply patch to affected area
- use 1 patch for up to 12 hours

children 12 years or younger:

- ask a doctor

INACTIVE INGREDIENT

Alpha Tocopherol Acetate, Aluminium Glycinate, Aluminium Hydroxide, Aluminium Sulphate, Borax, Carbomer, Collodial Silicon Dioxide, DMDM Hydantoin, Glycerine, Kaolin, Polyacrylic Acid, Polyvinyl Alcohol, Polyvinylpyrrolidone, Propylene Glycol, Purified Water, Sodium Carboxymethyl Cellulose, Sodium Ethylenediaminetetraacetic Acid, Sodium Polyacrylate, Sorbitol, Sorbitan Monooleate, Tartaric Acid & Titanium Dioxide.

QUESTIONS

Call +91-905-677-0088

DOSAGE AND ADMINISTRATION

Topical Patch for external use only

INDICATIONS AND USAGE

Temporarily relieves minor pain associated with: arthritis, simple backache, bursitis, tendonitis, muscle strains, sprains & bruises.